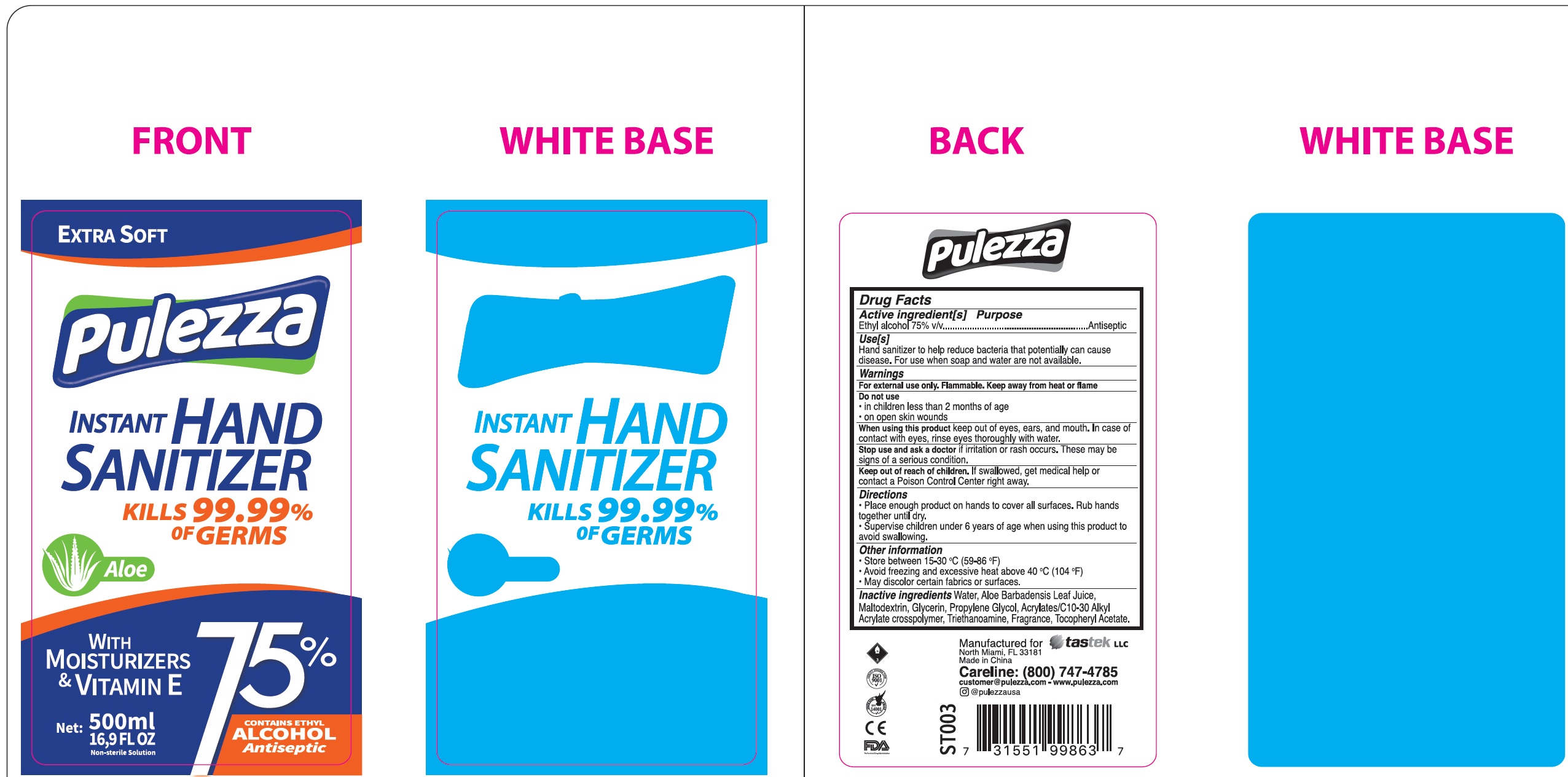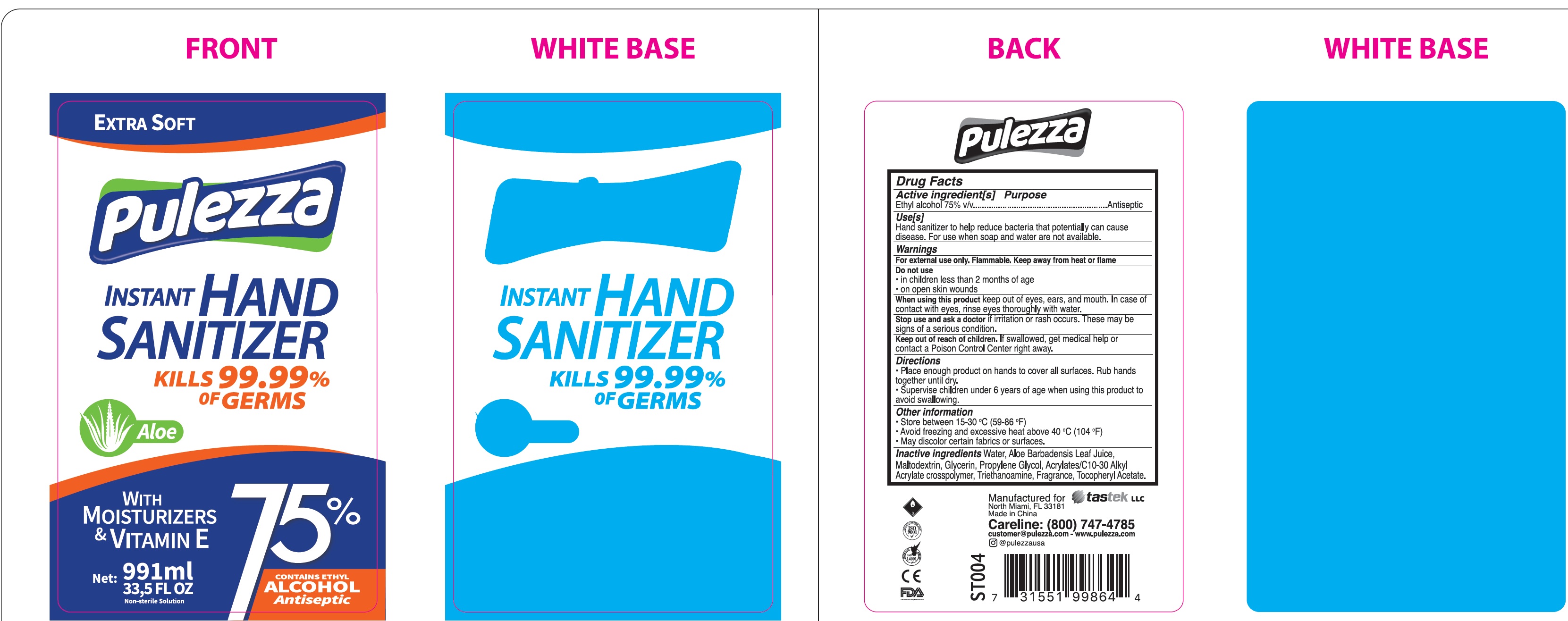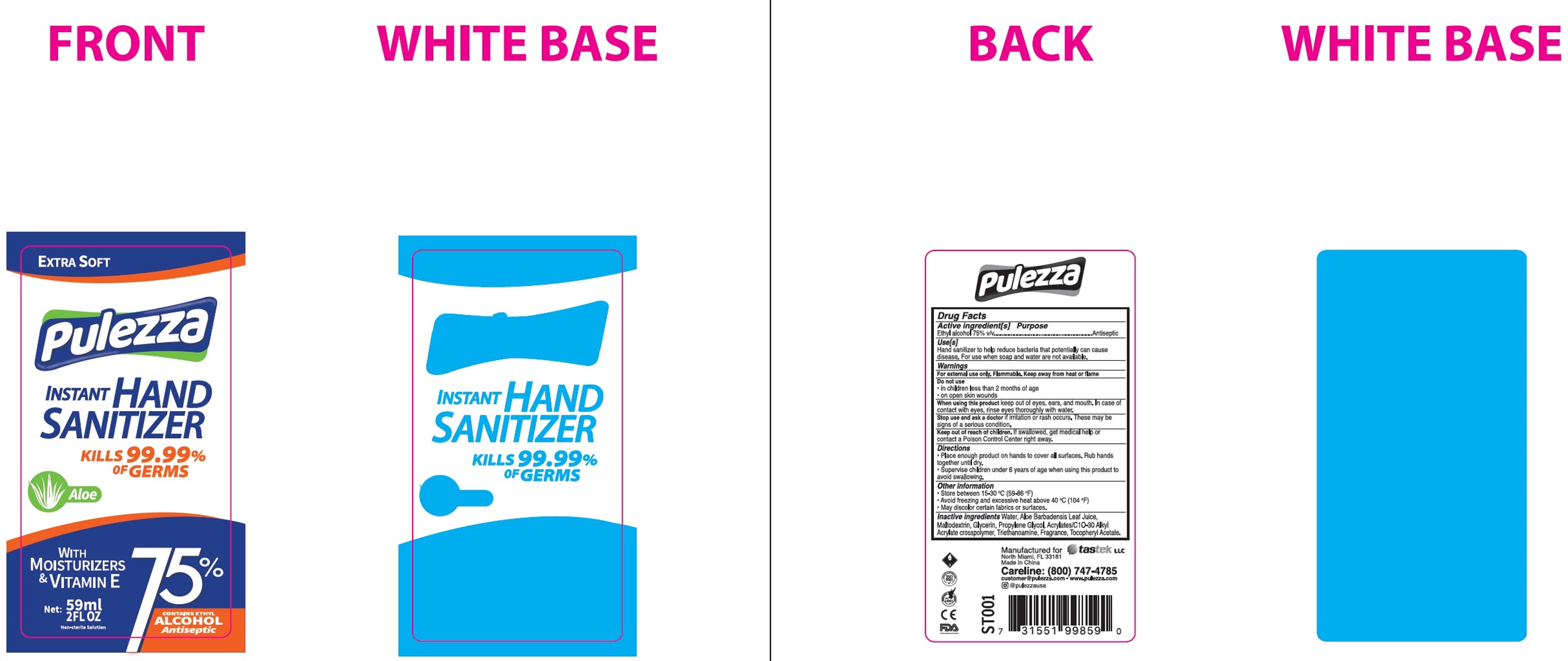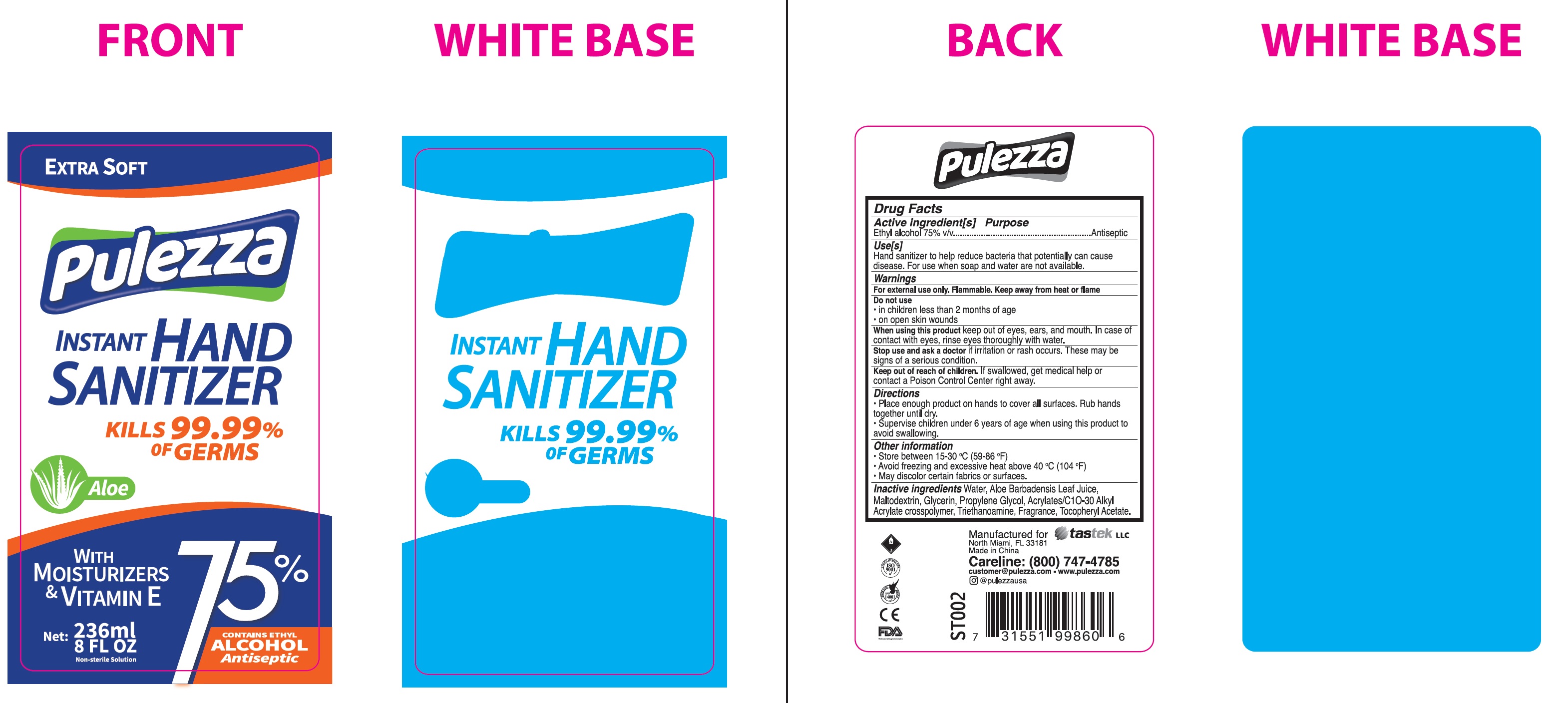 DRUG LABEL: Pulezza Instant Hand Sanitizer
NDC: 78702-000 | Form: GEL
Manufacturer: Tastek LLC
Category: otc | Type: HUMAN OTC DRUG LABEL
Date: 20200716

ACTIVE INGREDIENTS: ALCOHOL 0.75 mL/1 mL
INACTIVE INGREDIENTS: WATER; ALOE VERA LEAF; MALTODEXTRIN; GLYCERIN; PROPYLENE GLYCOL; CARBOMER INTERPOLYMER TYPE A (ALLYL SUCROSE CROSSLINKED); TROLAMINE; .ALPHA.-TOCOPHEROL ACETATE

Pulezza Instant Hand Sanitizer

Active ingredient[s]

Ethyl alcohol 75% v/v

Purpose

Antiseptic

Use[s]

Hand sanitizer to help reduce bacteria that potentially can cause disease. For use when soap and water are not available.

Warnings

For external use only. Flammable. Keep away from heat or flame

Do not use

- in children less than 2 months of age
- on open skin wounds

When using this product

keep out of eyes, ears, and mouth. In case of contact with eyes, rinse eyes thoroughly with water.

Stop use and ask a doctor

if irritation or rash occurs. These may be signs of a serious condition.

Keep out of reach of children.

If swallowed, get medical help or contact a Poison Control Center right away.

Directinos

- Place enough product on hands to cover all surfaces. Rub hands together until dry.
- Supervise children under 6 years of age when using this product to avoid swallowing.

Other information

- Store between 15-30 °C (59-86°F)
- Avoid freezing and excessive heat above 40 °C (104°F)
- May discolor certain fabrics or surfaces.

Inactive ingredients

Water, Aloe Barbadensis Leaf Juice, Maltodextrin, Glycerin, Propylene Glycol,Acrylates/C10-30 Alkyl Acrylate crosspolymer, Triethanoamine, Fragrance, Tocopheryl Acetate.